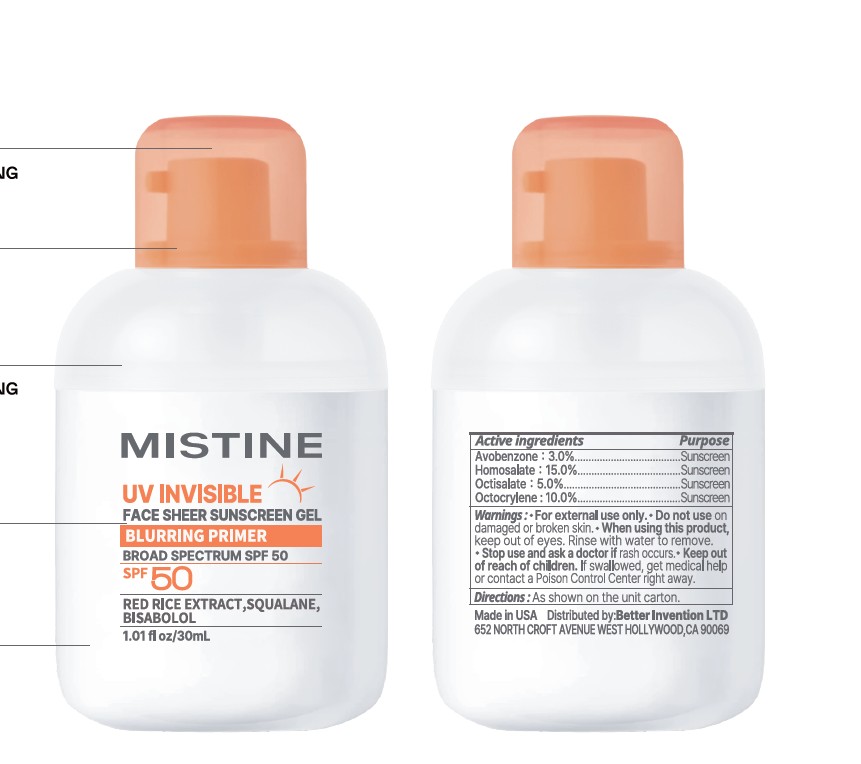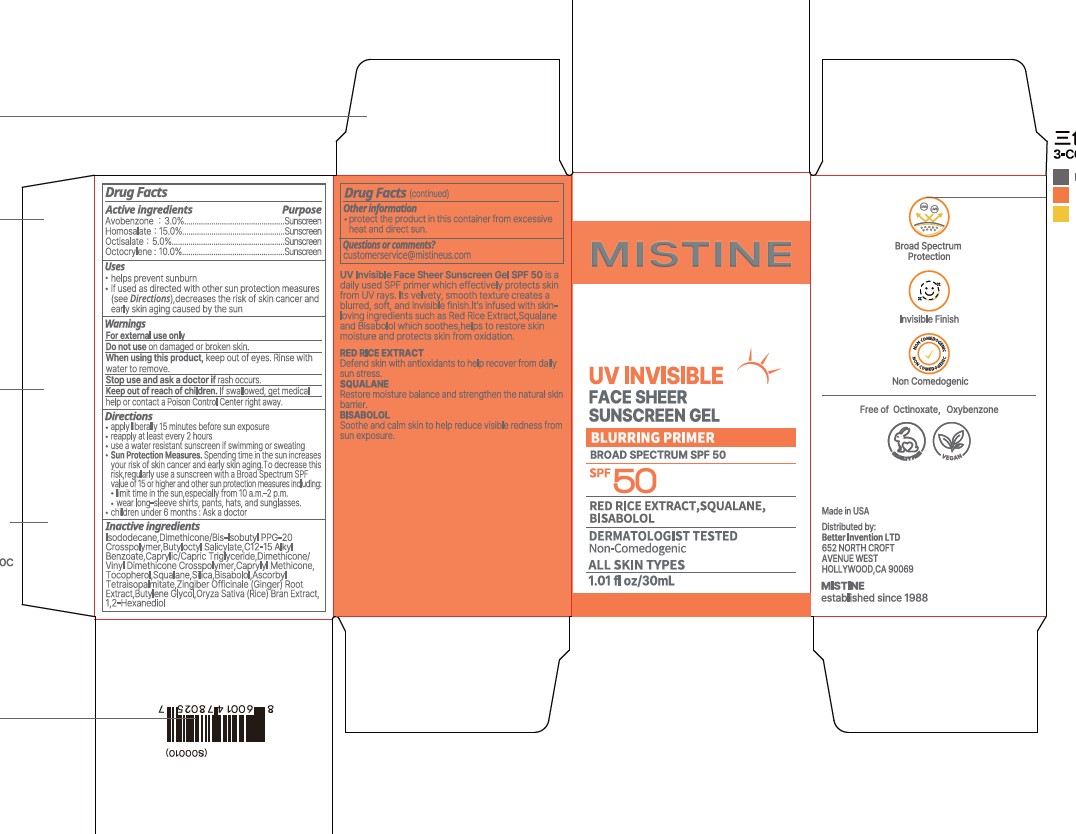 DRUG LABEL: MISTINE UV INVISIBLE FACE SHEER SUNSCREEN SPF 50
NDC: 87458-002 | Form: GEL
Manufacturer: BETTER INVENTION LTD
Category: otc | Type: HUMAN OTC DRUG LABEL
Date: 20260226

ACTIVE INGREDIENTS: AVOBENZONE 3 mg/100 mL; HOMOSALATE 15 mg/100 mL; OCTOCRYLENE 10 mg/100 mL; OCTISALATE 5 mg/100 mL
INACTIVE INGREDIENTS: BISABOLOL; ORYZA SATIVA (RICE) BRAN; CAPRYLIC/CAPRIC TRIGLYCERIDE; GINGER; DIMETHICONE/BIS-ISOBUTYL PPG-20 CROSSPOLYMER; SQUALANE; BUTYLENE GLYCOL; TOCOPHEROL; ISODODECANE; BUTYLOCTYL SALICYLATE; SILICA; ASCORBYL TETRAISOPALMITATE; CAPRYLYL METHICONE; DIMETHICONE/VINYL DIMETHICONE CROSSPOLYMER (SOFT PARTICLE); 1,2-HEXANEDIOL; C12-15 ALKYL BENZOATE

MISTINE UV INVISIBLE FACE SHEER SUNSCREEN GEL SPF 50

Active ingredients

Avobenzone: 3.0%

Homosalate: 15.0%

Octisalate: 5%

Octocrylene: 10%

Purpose

Sunscreen

USES

- help prevent sunburn
- if used as directed with other sun protection measures (see Directions), decreases the risk of skin cancer and early skin aging caused by the sun.

Warnings

For external use only

Do not use on damaged or broken skin

When using this product, keep out of eyes. Rinse with water to remove.

Stop use and ask a doctor if rash occurs.

Keep out of reach of children. If swallowed, get medical help or contact a Poison Control Center right away.

DIRECTIONS

- apply liberally 15 minutes before sun exposure
- reapply at least every 2 hours
- use a water resistant sunscreen if swimming or sweating
- Sun Protection Measures. Spending time in the sun increases your risk of skin cancer and early skin aging. To decrease this risk, regularly use a sunscreen with a Broad Spectrum SPF value of 15 or higher and other sun protection measures including:
- limit time in the sun, especially from 10 a.m. - 2 p.m.
- wear long-sleeve shirts, pants, hats, and sunglasses.
- children under 6 months: Ask a doctor

Inactive ingredients

Isododecane, Dimethicone/Bis-Isobutyl PPG-20 Crosspolymer, Butyloctyl Salicylate, C12-15 Alkyl Benzoate, Caprylic/Capric Triglyceride, Dimethicone/Vinyl Dimethicone Crosspolymer, Caprylyl Methicone, Tocopherol, Squalane, Silica, Bisabolol, Ascorbyl Tetraisopalmitate, Zingiber Officinale (Ginger) Root Extract, Butylene Glycol, Oryza Sativa (Rice) Bran Extract, 1,2-Hexanediol.

OTHER INFORMATION

- protect the prodict in this container from excessive heat and direct sun.

QUESTIONS OR COMMENTS

customerservice@mistineus.com